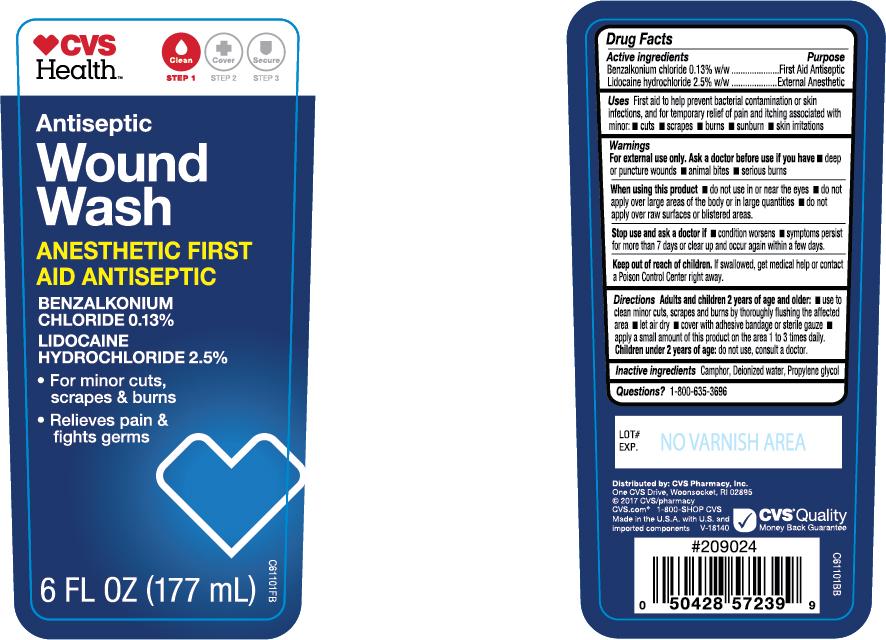 DRUG LABEL: CVS Health Antiseptic Wound Wash
NDC: 69842-925 | Form: RINSE
Manufacturer: CVS Pharmacy
Category: otc | Type: HUMAN OTC DRUG LABEL
Date: 20170706

ACTIVE INGREDIENTS: LIDOCAINE HYDROCHLORIDE 0.025 g/1 g; BENZALKONIUM CHLORIDE 0.0013 g/1 g
INACTIVE INGREDIENTS: CAMPHOR (SYNTHETIC); WATER; PROPYLENE GLYCOL

Drug Facts

Drug Facts

Active Ingredients

Benzalkonium Cl 0.13% w/w

Lidocaine HCl 2.5% w/w

Purpose

First aid antiseptic

Pain reliever

Uses

Firs aid to help prevent bacterial contamination or skin infections, and temporary relief of pain and itching associated with minor:

cuts
scrapes
burns
sunburns
skin irritations

Warnings

For external use only

Ask doctor before use if you have

deep or puncture wounds
animal bites
serious burns

When using this product

do not use near the eyes
do not apply over large areas of the body or in large quantities
do not apply over raw surfaces or blistered areas

Stop use and ask a doctor if

condition worsens
symptoms persist for more than 7 days, or clear up and occur again within a few days.

Keep out of reach of children.

If swallowed, get medical help or contact a Poison Control Center right away.

Directions

Adults and children 2 years and older:

clean the affected area
apply a small amount on the area 1 to 3 times daily.
may be covered with a sterile bandage
if bandaged, let dry first.

Other Information

Protect from excessive heat.

Questions or comments

1-800-635-3696

Inactive Ingredients

Camphor, Deionized Water, Propylene Glycol